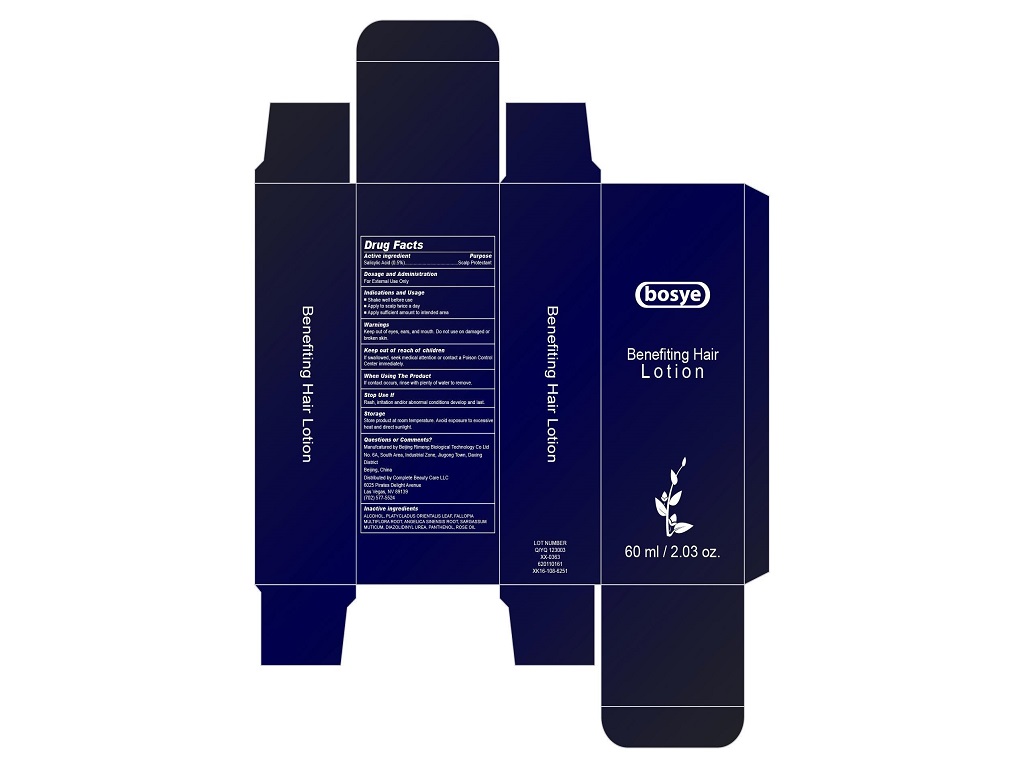 DRUG LABEL: Salicylic Acid
NDC: 47444-001 | Form: LOTION
Manufacturer: Bejing Rimeng Biological Technology Co Ltd
Category: otc | Type: HUMAN OTC DRUG LABEL
Date: 20251227

ACTIVE INGREDIENTS: SALICYLIC ACID 0.5 g/60 mL
INACTIVE INGREDIENTS: ALCOHOL; PLATYCLADUS ORIENTALIS LEAF; FALLOPIA MULTIFLORA ROOT; ANGELICA SINENSIS ROOT; SARGASSUM MUTICUM; DIAZOLIDINYL UREA; PANTHENOL; ROSE OIL

Bejing Rimeng Biological Technology Co Ltd

Active Ingredients

Salicylic Acid 0.5%

Purpose

Salicylic Acid Scalp Protectant

Dosage and Administration

For External Use Only.

Indications and Usage

■ Shake well before use

■ Apply to scalp twice a day

■ Apply sufficient amount to intended area

Warnings

Keep out of eyes, ears, and mouth. Do not use on damaged or broken skin.

Keep out of reach of children.

If swallowed, get medical help or contact a Poison Control Center immediately.

When Using the Product

If contact occurs, rinse with plenty of water to remove.

Stop Use If

Rash, irritation and/or abnormal reaction develop and last.

Storage

Store product at room temperature. Avoid exposure to excessive heat and direct sunlight.

Questions or Comments?

Manufactured by Beijing Rimeng Biological Technology Co Ltd

No. 6A, South Area, Industrial Zone, Jiugong Town, Daxing District

Beijing, China

Distributed by Complete Beauty Care LLC

6025 Pirates Delight Avenue

Las Vegas, NV 89139

(702)577-5524

Inactive Ingredients

ALCOHOL, PLATYCLADUS ORIENTALIS LEAF, FALLOPIA MULTIFLORA ROOT, ANGELICA SINENSIS ROOT, SARGASSUM MUTICUM, DIAZOLIDINYL UREA, PANTHENOL, ROSE OIL